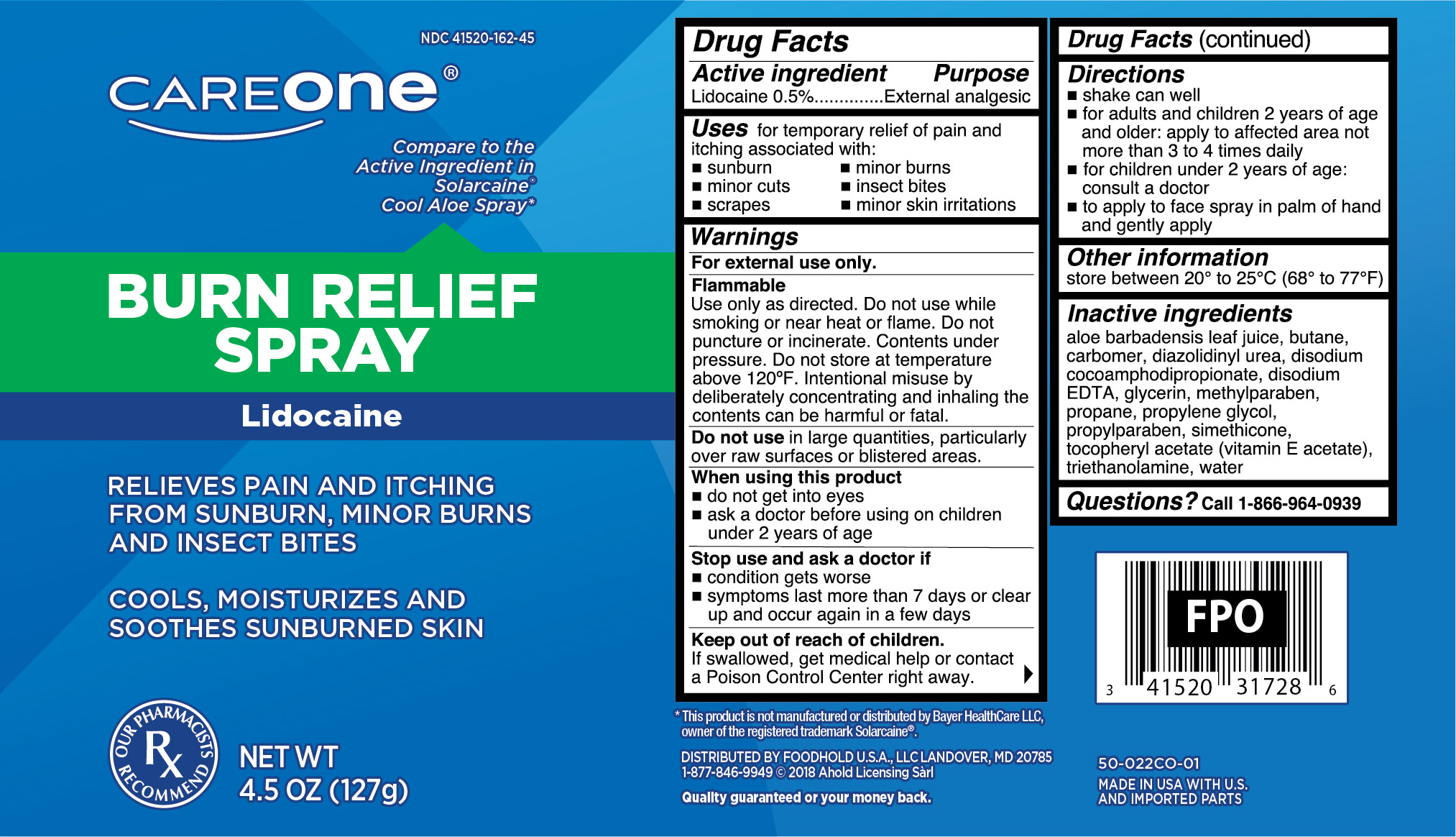 DRUG LABEL: Lidocaine
NDC: 41520-162 | Form: AEROSOL, SPRAY
Manufacturer: Foodhold USA
Category: otc | Type: HUMAN OTC DRUG LABEL
Date: 20251027

ACTIVE INGREDIENTS: LIDOCAINE 0.64 g/127 g
INACTIVE INGREDIENTS: BUTANE; CARBOMER COPOLYMER TYPE A; DIAZOLIDINYL UREA; ALOE VERA LEAF; DISODIUM COCOAMPHODIPROPIONATE; EDETATE DISODIUM; GLYCERIN; METHYLPARABEN; PROPANE; PROPYLENE GLYCOL; .ALPHA.-TOCOPHEROL ACETATE; TROLAMINE; WATER

Burn Relief Spray

Active Ingredients

Lidocaine 0.5%

Purpose

External analgesic

Uses

for temporary relief of pain and itching associated with:

- sunburn
- minor burns
- minor cuts
- insect bites
- scrapes
- minor skin irritations

Warnings

For external use only.

Flammable:

Use only as directed. Do not use while smoking or near heat or flame. Do not puncture or incinerate. Contents under pressure. Do not store at temperature above 120ºF. Intentional misuse by delibrately concentrating and inhaling the contents can be harmul or fatal.

Do not use

in large quantities, particularly over raw surfaces or blistered areas.

When using this product

- do not get into eyes
- ask a doctor before using on children under 2 years of age

Stop use and ask a doctor if

- condition gets worse
- symptoms last more than 7 days or clear up and occur again in a few days

Keep out of reach of children.

If swallowed, get medical help or contact a Poison Control Center right away.

Directions

- shake can well
- for adults and children 2 years of age and older: apply to affected area not more than 3 to 4 times daily
- for children under 2 years of age: consult a doctor
- to apply to face spray in palm of hand and gently apply

Other information

store between 20º to 25ºC (68º to 77ºF)

Inactive ingredients

aloe barbadensis leaf juice, butane, carbomer, diazolidinyl urea, disodium cocoamphodipropionate, disodium EDTA, glycerine, methylparaben, propane, propylene glycol, propylparaben, simethicone, tocopheryl acetate (vitamin E acetate), triethanolamine, water

Questions?

Call 1-866-964-0939

Principal Display Panel

CareOne

Burn Relief Spray

Lidocaine

Relieves Pain and Itching from Sunburn, Minor Burns and Insect Bites

Cools, Moisturizes and Soothes Sunburned Skin

NET WT 4.5 OZ (127g)